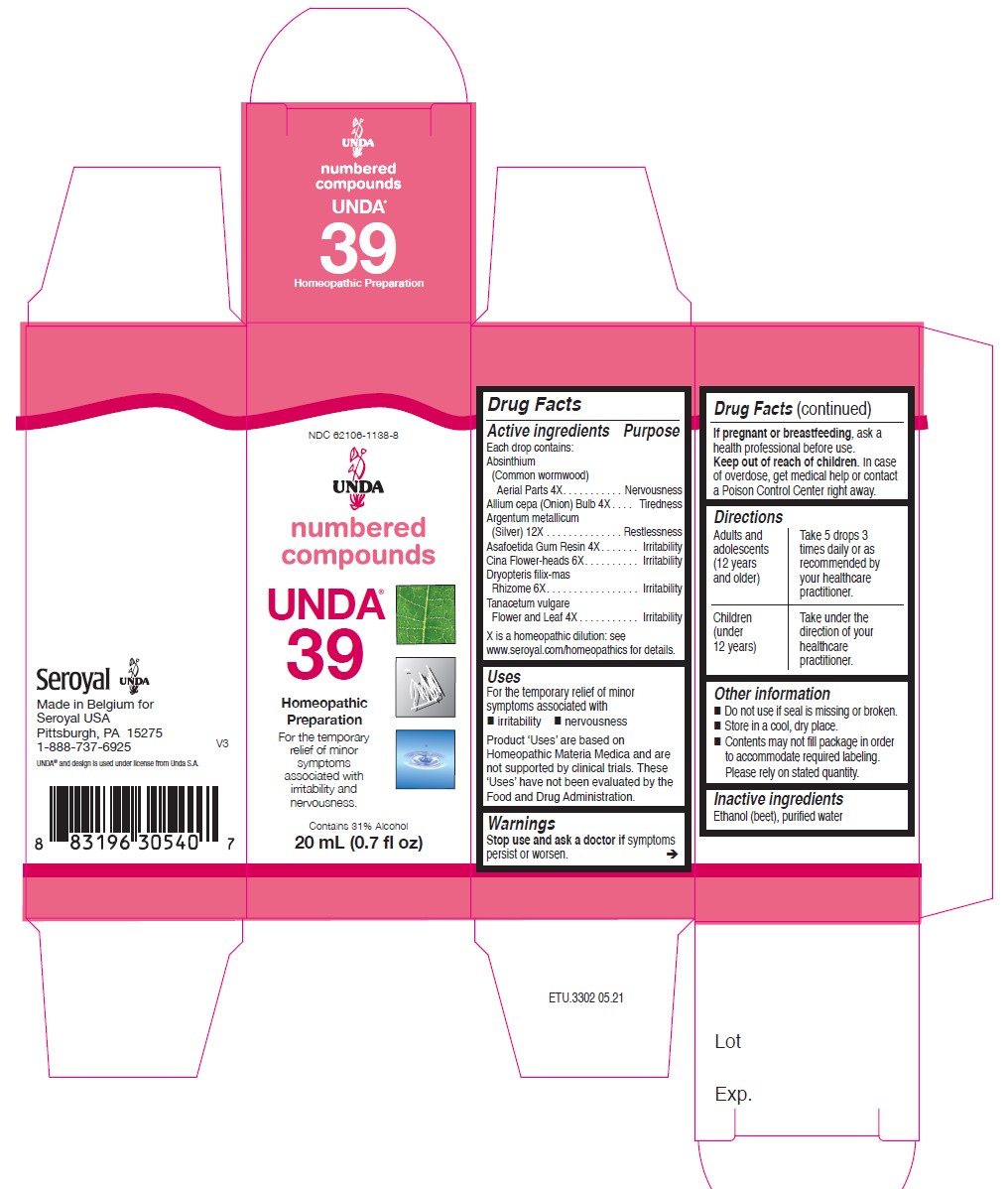 DRUG LABEL: Unda 39
NDC: 62106-1138 | Form: LIQUID
Manufacturer: Seroyal USA
Category: homeopathic | Type: HUMAN OTC DRUG LABEL
Date: 20221025

ACTIVE INGREDIENTS: DRYOPTERIS FILIX-MAS ROOT 6 [hp_X]/20 mL; ARTEMISIA CINA PRE-FLOWERING TOP 6 [hp_X]/20 mL; SILVER 12 [hp_X]/20 mL; ASAFETIDA 4 [hp_X]/20 mL; WORMWOOD 4 [hp_X]/20 mL; ONION 4 [hp_X]/20 mL; TANACETUM VULGARE TOP 4 [hp_X]/20 mL
INACTIVE INGREDIENTS: ALCOHOL; WATER

Unda 39

Active ingredients
Each drop contains:
Absinthium (Common wormwood) Aerial Parts 4X
Allium cepa (Onion) Bulb 4X
Argentum metallicum (Silver) 12X
Asafoetida Gum Resin 4X
Cina Flower-heads 6X
Dryopteris filix-mas Rhizome 6X
Tanacetum vulgare Flower and Leaf 4X

Uses

For the temporary relief of minor symptoms associated with
irritability and anxiousness.

Warnings
If pregnant or breastfeeding, ask a health professional before use.

Keep out of reach of children.

In case of overdose, get medical help or contact a
Poison Control Center right away.

Stop use and ask a doctor if symptoms persist or worsen.

PREGNANCY OR BREAST FEEDING

If pregnant or breastfeeding, ask a health professional before use.

Keep out of reach of children.

OVERDOSAGE

In case of overdose, get medical help or contact a
Poison Control Center right away.

Inactive Ingredients:

Ethanol (beet),
purified water

Directions

Adults and adolescents (12 years and older)

Take 5 drops three times daily or as recommended by your healthcare practitioner.

Children (under 12 years)

Take under the direction of your healthcare practitioner.

Uses

For the temporary relief of minor symptoms
associated with irritability and anxiousness.

Directions

Adults and adolescents (12 years and older)

Take 5 drops three times daily or as recommended by your healthcare practitioner.

Children (under 12 years)

Take under the direction of your healthcare practitioner.

Other information
Do not use if seal is missing or broken.
Store in a cool, dry place.

PACKAGE LABEL

NDC 62106-1138-8

UNDA

numbered compounds

UNDA 39

Homeopathic Preparation

For the temporary relief of minor
symptoms associated with
irritability and anxiousness.

Contains 31% Alcohol
0.7 fl oz (20 ml)